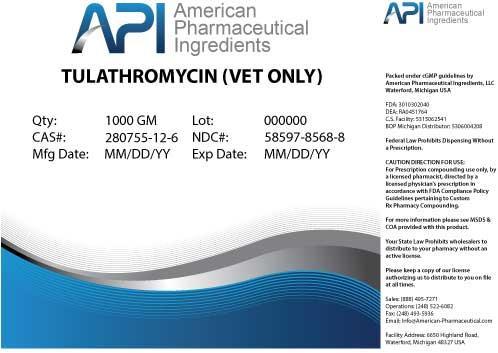 DRUG LABEL: TULATHROMYCIN
NDC: 58597-8568 | Form: POWDER
Manufacturer: AMERICAN PHARMACEUTICAL INGREDIENTS LLC
Category: other | Type: BULK INGREDIENT
Date: 20140502

ACTIVE INGREDIENTS: TULATHROMYCIN 1 g/1 g

TULATHROMYCIN